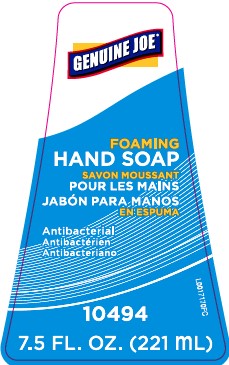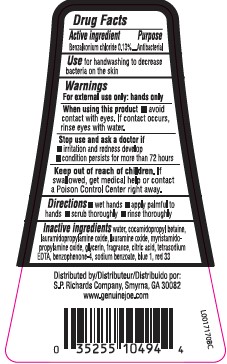 DRUG LABEL: Benzalkonium chloride
NDC: 62832-628 | Form: LIQUID
Manufacturer: S. P. Richards Company
Category: otc | Type: HUMAN OTC DRUG LABEL
Date: 20260218

ACTIVE INGREDIENTS: BENZALKONIUM CHLORIDE 1.3 mg/1 mL
INACTIVE INGREDIENTS: COCAMIDOPROPYL BETAINE; WATER; LAURAMIDOPROPYLAMINE OXIDE; LAURAMINE OXIDE; MYRISTAMIDOPROPYLAMINE OXIDE; GLYCERIN; CITRIC ACID MONOHYDRATE; EDETATE SODIUM; SODIUM BENZOATE; FD&C BLUE NO. 1; D&C RED NO. 33

Genuine Joe 628.002/628AD-AE
Antibacterial Foaming Hand Wash

Active ingredient

Benzalkonium chloride 0.13%

Purpose

Antibacterial

Use

for handwashing to decrease bacteria on the skin

Warnings

For external use only: hands only

When using this product

- avoid contact with eyes. If contact occurs, rinse eyes thoroughly with water.

Stop use and ask a doctor if

- irritation and redness develop
- condition persists for more than 72 hours

Keep out of reach of children.

If swallowed, get medical help or contact a Poison Control Center right away.

Directions

- wet hands
- apply palmful to dry hands
- scrub thoroughly
- rinse thoroughly

Inactive ingredients

water, cocamidopropyl betaine, lauramidopropylamine oxide, lauramine oxide, myristamidopropylamine oxide, glycerin, fragrance, citric acid, tetrasodium EDTA, benzophenone-4, sodium benzoate, blue 1, red 33

ADVERSE REACTION

Distributed by

S.P. Rochards Company, Smyrna, GA 30082

www.genuinejoe.com

principal display panel

GENUINE JOE®

FOAMING HAND SOAP

Antibacterial

7.5 FL OZ (221 mL)